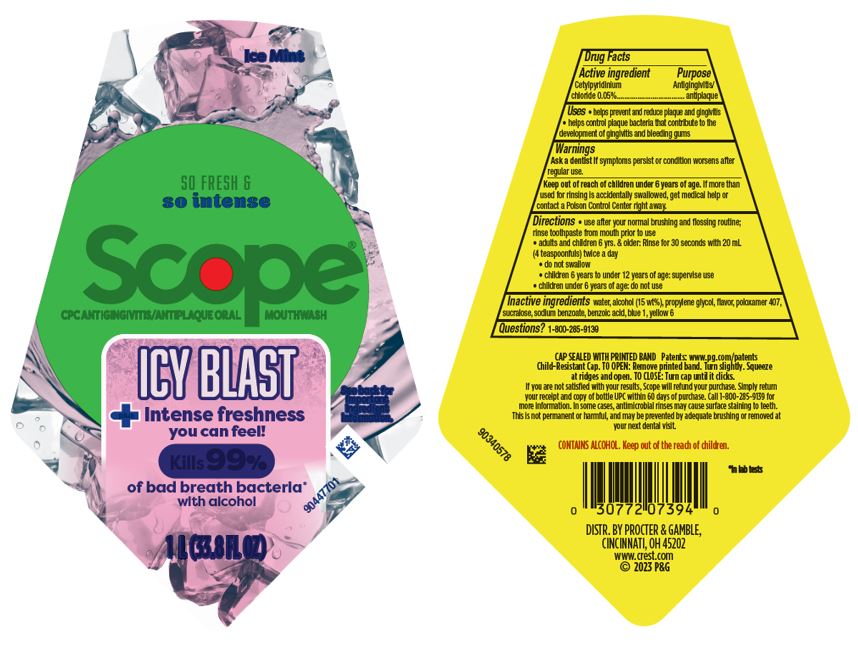 DRUG LABEL: Scope
NDC: 69423-666 | Form: RINSE
Manufacturer: The Procter & Gamble Manufacturing Company
Category: otc | Type: HUMAN OTC DRUG LABEL
Date: 20250806

ACTIVE INGREDIENTS: CETYLPYRIDINIUM CHLORIDE 0.05 g/1 mL
INACTIVE INGREDIENTS: ALCOHOL; WATER; PROPYLENE GLYCOL; POLOXAMER 407; SODIUM BENZOATE; BENZOIC ACID; SUCRALOSE; FD&C BLUE NO. 1; FD&C YELLOW NO. 6

Scope Icy Blast

Drug Facts

Active ingredient

Cetylpyridinium chloride 0.05%

Purpose

Antigingivitis/Antiplaque

Uses

- helps prevent and reduce plaque and gingivitis
- helps control plaque bacteria that contribute to the development of gingivitis and bleeding gums

Warning

WARNINGS

Ask a dentist if symptoms persist or condition worsens after regular use.

Keep out of reach of children 6 years of age.If more than used for rinsing is accidentally swallowed, get medical help or contact a Poison Control Center right away.

Directions

- use after your normal brushing and flossing routine, rinse toothpaste from mouth prior to use
- adults and children 6 yrs. & older: Rinse for 30 seconds with 20 mL (4 teaspoonfuls) twice a day
- do not swallow
- children 6 years to under 12 years of age: supervise use
- children under 6 years of age: do not use

Questions?

1-800-285-9139

Inactive ingredients

water, alcohol (15 wt%), propylene glycol, flavor, poloxamer 407, sucralose, sodium benzoate, benzoic acid, blue 1, yellow 6

DISTR. BY PROCTER & GAMBLE,

CINCINNATI, OH 45202

Principal Display Panel 1L bottle

Ice Mint

SO FRESH &

so intense

Scope

CPC ANTIGINGIVITIS/ANTIPLAQUE MOUTHWASH

ICY BLAST

plus Intense freshness

you can feel!

Kills 99%

of bad breath bacteria

with alcohol

1 L (33.8 FL OZ)